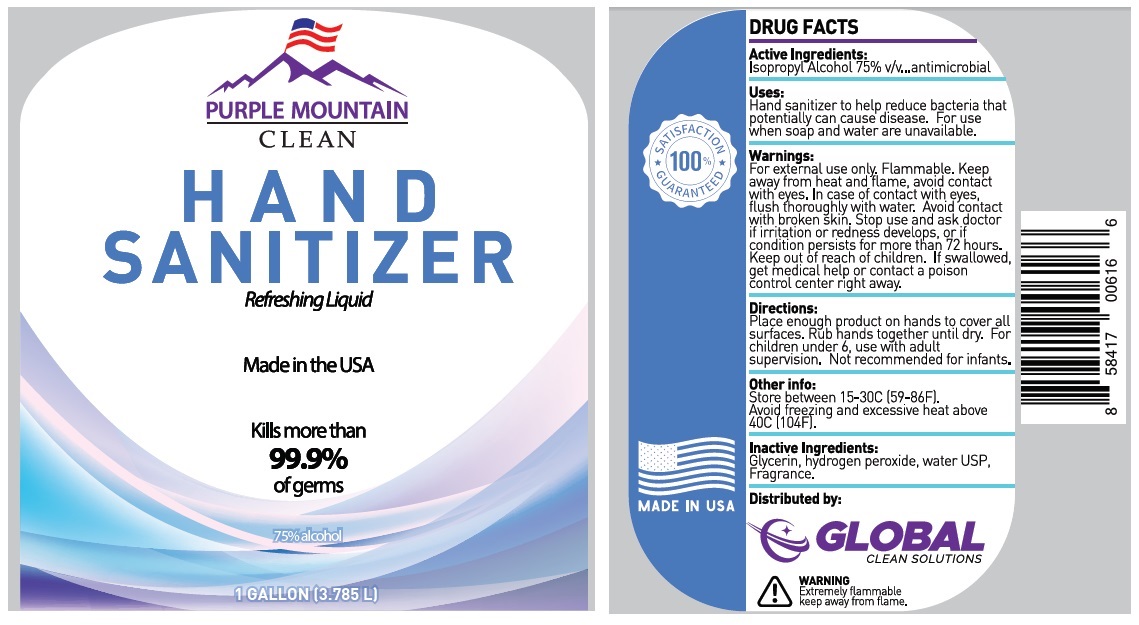 DRUG LABEL: Purple Mountain Clean Hand Sanitizer
NDC: 80120-102 | Form: LIQUID
Manufacturer: Edison Nation, Inc.
Category: otc | Type: HUMAN OTC DRUG LABEL
Date: 20200820

ACTIVE INGREDIENTS: ISOPROPYL ALCOHOL 75 L/100 L
INACTIVE INGREDIENTS: GLYCERIN; HYDROGEN PEROXIDE; WATER

PURPLE MOUNTAIN CLEAN HAND SANITIZER

Active Ingredients:

Isopropyl Alcohol 75% v/v

Purpose:

antimicrobial

Uses:

Hand sanitizer to help reduce bacteria that potentially can cause disease. For use when soap and water are unavailable.

Warnings:

For external use only. Flammable. Keep away from heat and flame, avoid contact with eyes. In case of contact with eyes, flush thoroughly with water. Avoid contact with broken skin. Stop use and ask doctor if irritation or redness develops, or if condition persists for more than 72 hours

Keep out of reach of children. If swallowed, get medical help or contact a poison control center right away.

Directions:

Place enough product on hands to cover all surfaces. Rub hands together until dry. For children under 6, use with adult supervision. Not recommended for infants.

Other info:

Store between 15-30C (59-86F).

Avoid freezing and excessive heat above 40C (104F).

Inactive Ingredients:

Glycerin, hydrogen peroxide, water USP, Fragrance

Refreshing Liquid

Made in the USA

Kills more than 99.9% of germs

75% alcohol

100% SATISFACTION

GUARANTEED

Distributed by:

GLOBAL CLEAN SOLUTIONS

WARNING

Extremely flammable